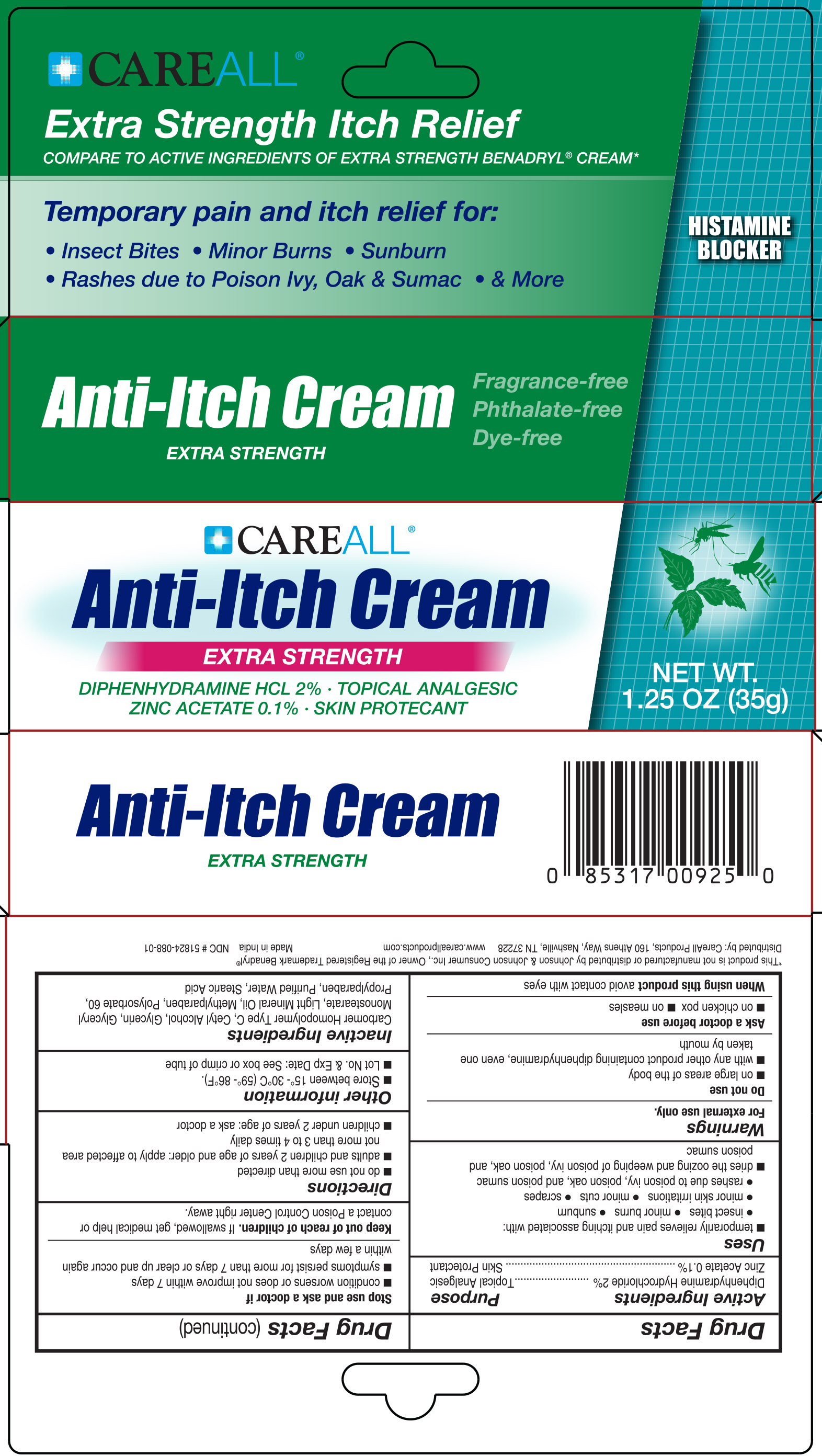 DRUG LABEL: CAREALL Anti-Itch
NDC: 51824-088 | Form: CREAM
Manufacturer: New World Imports, Inc
Category: otc | Type: HUMAN OTC DRUG LABEL
Date: 20251201

ACTIVE INGREDIENTS: DIPHENHYDRAMINE HYDROCHLORIDE 20 mg/1 g; ZINC ACETATE 1 mg/1 g
INACTIVE INGREDIENTS: CARBOMER HOMOPOLYMER TYPE C (ALLYL PENTAERYTHRITOL CROSSLINKED); CETYL ALCOHOL; GLYCERYL MONOSTEARATE; GLYCERIN; METHYLPARABEN; PROPYLPARABEN; LIGHT MINERAL OIL; POLYSORBATE 60; STEARIC ACID; WATER

Active Ingredients

Diphenhydramine Hydrochloride 2%

Zinc Acetate 0.1%

Purpose

Diphenhydramine Hydrochloride 2%....Topical Analgesic

Zinc Acetate 0.1%.............................Skin Protectant

Keep out of reach of children. If swallowed, get medical help or contact a Poison Control Center right away.

Uses

- temporarily relieves pain and itching associated with: insect bites, minor burns, sunburn, minor skin irritations, minor cuts, scrapes, rashes due to poison ivy / poison oak / poison sumac.
- dries the oozing and weeping of poison ivy, poison oak and poison sumac.

Warnings

For external use only.

Due not use:

- on large areas of the body
- with any other product containing diphenhydramine, even one taken by mouth.

Ask a doctor before use:

- on chicken pox
- on measles

When using this productavoid contact with eyes

Stop use and ask a doctor if:

- condition worsens or does not improve within 7 days
- symptoms persists for more than 7 days or clear up and occur again within a few days

Directions

- do not use more than directed
- adults and children 2 years of age and older: apply to affected area not more than 3 to 4 times daily
- children under 2 years of age: ask a doctor

Inactive Ingredients

carbomer homopolymer type c, cetyl alcohol, glycerin, glyceryl monostearate, light mineral oil, methylparaben, polysorbate 60, propylparaben, purified water, stearic acid